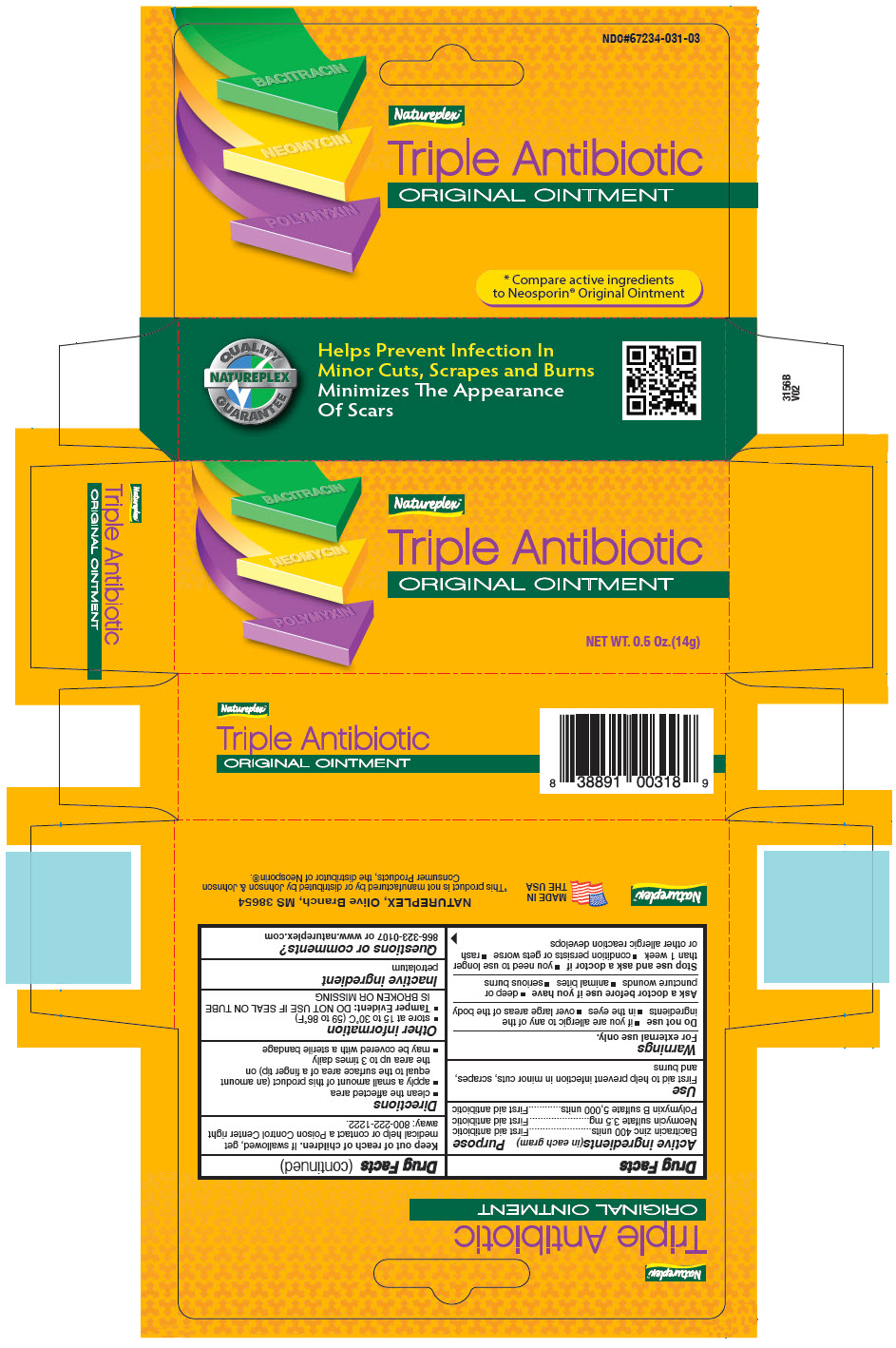 DRUG LABEL: TRIPLE ANTIBIOTIC 
NDC: 67234-031 | Form: OINTMENT
Manufacturer: Natureplex LLC
Category: otc | Type: HUMAN OTC DRUG LABEL
Date: 20260212

ACTIVE INGREDIENTS: BACITRACIN ZINC 400 U/9.4 g; NEOMYCIN SULFATE 3.5 mg/9.4 g; POLYMYXIN B SULFATE 5000 U/9.4 g
INACTIVE INGREDIENTS: PETROLATUM

TRIPLE ANTIBIOTIC
FIRST AID ANTIBIOTIC

Drug Facts

ACTIVE INGREDIENT

Active ingredients(in each gram) | Purpose
Bacitracin zinc 400 units | First aid antibiotic
Neomycin sulfate 3.5 mg | First aid antibiotic
Polymyxin B sulfate 5,000 units | First aid antibiotic

Use

First aid to help prevent infection in minor cuts, scrapes, and burns

Warnings

For external use only.

Do not use

- if you are allergic to any of the ingredients
- in the eyes
- over large areas of the body

Ask a doctor before use if you have

- deep or puncture wounds
- animal bites
- serious burns

Stop use and ask a doctor if

- you need to use longer than 1 week
- condition persists or gets worse
- rash or other allergic reaction develops

Keep out of reach of children. If swallowed, get medical help or contact a Poison Control Center right away: 800-222-1222.

Directions

- clean the affected area
- apply a small amount of this product (an amount equal to the surface area of a finger tip) on the area up to 3 times daily
- may be covered with a sterile bandage

Other information

- store at 15 to 30°C (59 to 86°F)
- Tamper Evident: DO NOT USE IF FLAPS ON CARTON ARE NOT SEALED OR MISSING

Inactive ingredient

petrolatum

Questions or comments?

866-323-0107 or www.natureplex.com

PRINCIPAL DISPLAY PANEL - 14 g Tube Carton

BACITRACIN

NEOMYCIN

POLYMYXIN

Natureplex™
Triple Antibiotic
ORIGINAL OINTMENT

NET WT. 0.5 Oz. (14g)